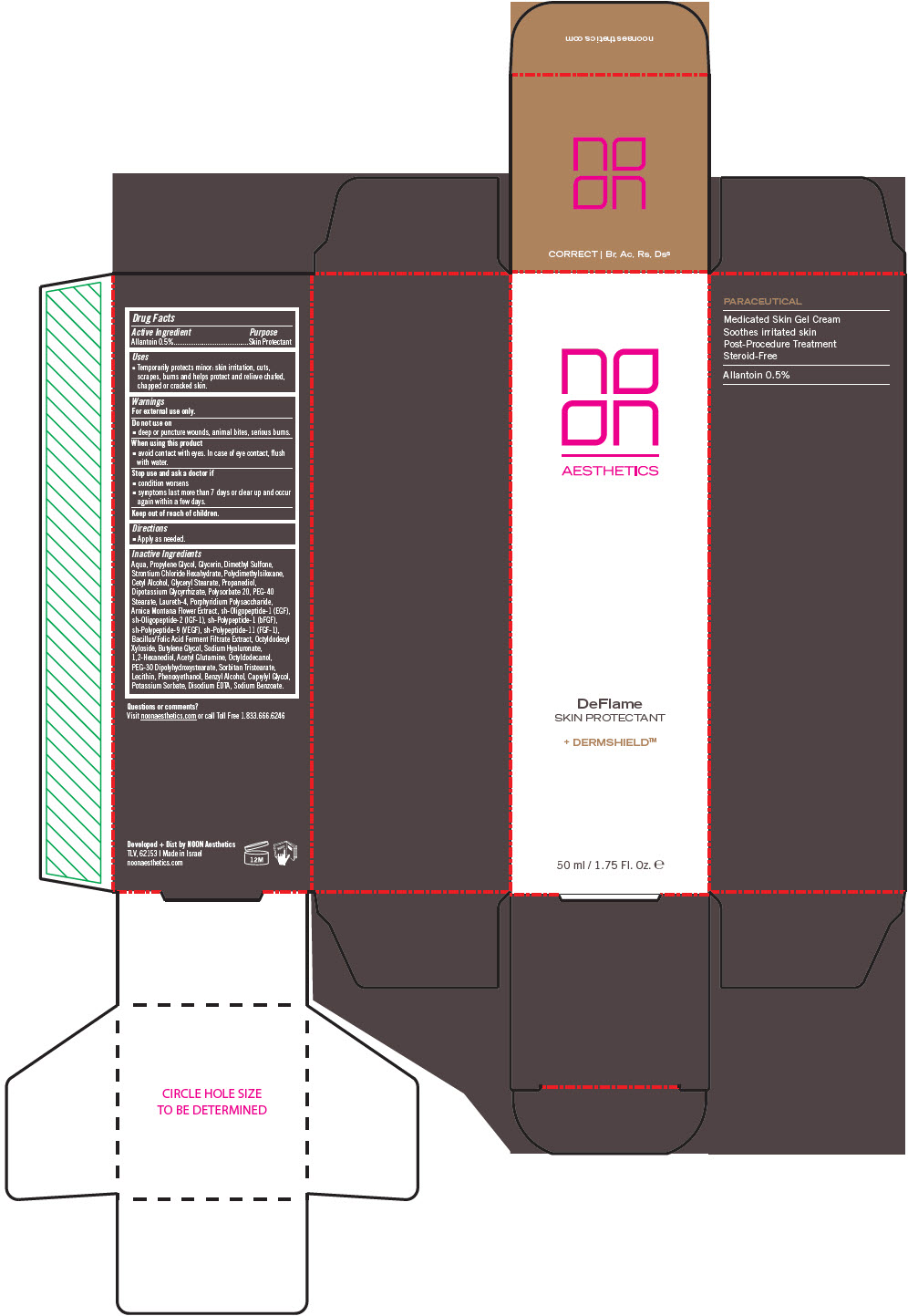 DRUG LABEL: DeFlame
NDC: 78863-1270 | Form: CREAM
Manufacturer: Noon Aesthetics M.R. Ltd
Category: otc | Type: HUMAN OTC DRUG LABEL
Date: 20250114

ACTIVE INGREDIENTS: ALLANTOIN 5 mg/1 mL
INACTIVE INGREDIENTS: WATER; PROPYLENE GLYCOL; GLYCERIN; DIMETHYL SULFONE; STRONTIUM CHLORIDE HEXAHYDRATE; DIMETHICONE; CETYL ALCOHOL; GLYCERYL MONOSTEARATE; PROPANEDIOL; GLYCYRRHIZINATE DIPOTASSIUM; POLYSORBATE 20; LAURETH-4; ARNICA MONTANA FLOWER; OCTYLDODECYL XYLOSIDE; BUTYLENE GLYCOL; HYALURONATE SODIUM; 1,2-HEXANEDIOL; ACEGLUTAMIDE; OCTYLDODECANOL; PEG-30 DIPOLYHYDROXYSTEARATE (4000 MW); SORBITAN TRISTEARATE; PHENOXYETHANOL; BENZYL ALCOHOL; CAPRYLYL GLYCOL; POTASSIUM SORBATE; EDETATE DISODIUM ANHYDROUS; SODIUM BENZOATE

DeFlame

Drug Facts

Active Ingredient

Allantoin 0.5%

Purpose

Skin Protectant

Uses

- Temporarily protects minor: skin irritation, cuts, scrapes, burns and helps protect and relieve chafed, chapped or cracked skin.

Warnings

For external use only.

Do not use on

- deep or puncture wounds, animal bites, serious burns.

When using this product

- avoid contact with eyes. In case of eye contact, flush with water.

Stop use and ask a doctor if

- condition worsens
- symptoms last more than 7 days or clear up and occur again within a few days.

Keep out of reach of children.

Directions

- Apply as needed.

Inactive Ingredients

Aqua, Propylene Glycol, Glycerin, Dimethyl Sulfone, Strontium Chloride Hexahydrate, Polydimethylsiloxane, Cetyl Alcohol, Glyceryl Stearate, Propanediol, Dipotassium Glycyrrhizate, Polysorbate 20, PEG-40 Stearate, Laureth-4, Porphyridium Polysaccharide, Arnica Montana Flower Extract, sh-Oligopeptide-1 (EGF), sh-Oligopeptide-2 (IGF-1), sh-Polypeptide-1 (bFGF), sh-Polypeptide-9 (VEGF), sh-Polypeptide-11 (FGF-1), Bacillus/Folic Acid Ferment Filtrate Extract, Octyldodecyl Xyloside, Butylene Glycol, Sodium Hyaluronate, 1,2-Hexanediol, Acetyl Glutamine, Octyldodecanol, PEG-30 Dipolyhydroxystearate, Sorbitan Tristearate, Lecithin, Phenoxyethanol, Benzyl Alcohol, Caprylyl Glycol, Potassium Sorbate, Disodium EDTA, Sodium Benzoate.

Questions or comments?

Visit noonaesthetics.com or call Toll Free 1.833.666.6246

Dist by NOON Aesthetics
TLV, 62153

PRINCIPAL DISPLAY PANEL - 50 ml Tube Carton

noon
AESTHETICS

DeFlame
SKIN PROTECTANT

+ DERMSHIELD™

50 ml / 1.75 Fl. Oz. e